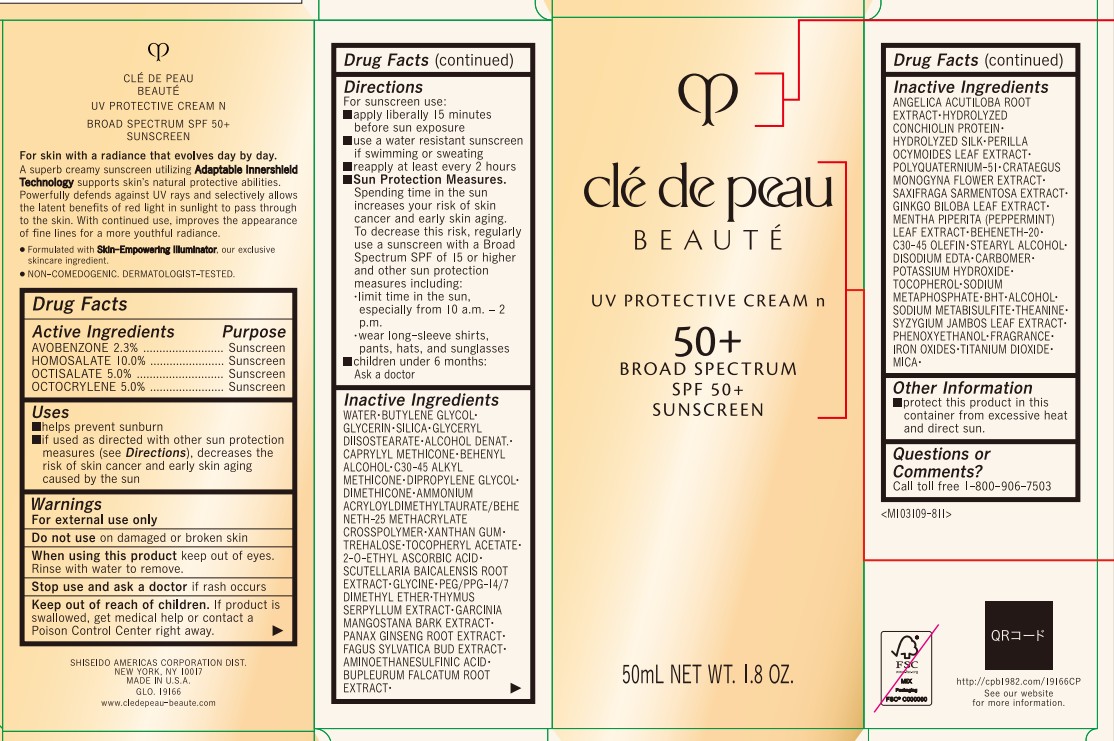 DRUG LABEL: cle de peau BEAUTE UV PROTECTIVE N
NDC: 58411-955 | Form: CREAM
Manufacturer: Shiseido Americas Corporation
Category: otc | Type: HUMAN OTC DRUG LABEL
Date: 20251216

ACTIVE INGREDIENTS: AVOBENZONE 1.7825 g/50 mL; HOMOSALATE 7.75 g/50 mL; OCTISALATE 3.875 g/50 mL; OCTOCRYLENE 3.875 g/50 mL
INACTIVE INGREDIENTS: WATER; BUTYLENE GLYCOL; GLYCERIN; SILICA; GLYCERYL DIISOSTEARATE; ALCOHOL; CAPRYLYL METHICONE; DIPROPYLENE GLYCOL; DIMETHICONE; AMMONIUM ACRYLOYLDIMETHYLTAURATE/BEHENETH-25 METHACRYLATE CROSSPOLYMER (52000 MPA.S); XANTHAN GUM; TREHALOSE; .ALPHA.-TOCOPHEROL ACETATE; 2-O-ETHYL ASCORBIC ACID; SCUTELLARIA BAICALENSIS ROOT; GLYCINE; PEG/PPG-14/7 DIMETHYL ETHER; THYMUS SERPYLLUM; GARCINIA MANGOSTANA BARK; PANAX GINSENG ROOT; FAGUS SYLVATICA FLOWER BUD; AMINOETHANESULFINIC ACID; BUPLEURUM FALCATUM ROOT; ANGELICA ACUTILOBA ROOT; PERILLA OCYMOIDES SEED OIL; POLYQUATERNIUM-51 (2-METHACRYLOYLOXYETHYL PHOSPHORYLCHOLINE/N-BUTYL METHACRYLATE; 3:7); CRATAEGUS MONOGYNA FLOWER; GINKGO BILOBA LEAF; MENTHA PIPERITA (PEPPERMINT) LEAF; BEHENETH-20; C30-45 OLEFIN; STEARYL ALCOHOL; EDETATE DISODIUM; CARBOMER; POTASSIUM HYDROXIDE; TOCOPHEROL; SODIUM METAPHOSPHATE; BUTYLATED HYDROXYTOLUENE; SODIUM METABISULFITE; THEANINE; SYZYGIUM JAMBOS LEAF; PHENOXYETHANOL; FERRIC OXIDE RED; TITANIUM DIOXIDE; MICA

cle de peau BEAUTE UV PROTECTIVE N

Drug Facts

Active Ingredients | Purpose
Avobenzone 2.3% | Sunscreen
Homosalate 10.0% | Sunscreen
Octisalate 5.0% | Sunscreen
Octocrylene 5.0% | Sunscreen

Uses

- helps prevent sunburn
- if used as directed with other sun protection measures (see Directions), decreases the risk of skin cancer and early skin aging caused by the sun

Warnings

For external use only

Do not use on damaged or broken skin

When using this product keep out of eyes. Rinse with water to remove.

Stop use and ask a doctor if rash occurs

Keep out of reach of children. If product is swallowed, get medical help or contact a Poison Control Center right away.

Directions

For sunscreen use:

- apply liberally 15 minutes before sun exposure
- use a water resistant sunscreen if swimming or sweating
- reapply at least every 2 hours
- Sun Protection Measures. Spending time in the sun increases your risk of skin cancer and early skin aging. To decrease this risk, regularly use a sunscreen with a Broad Spectrum SPF of 15 or higher and other sun protection measures including:

• limit time in the sun, especially from 10 a.m. - 2 p.m.

• wear long-sleeve shirts, pants, hats, and sunglasses

- children under 6 months: Ask a doctor

INACTIVE INGREDIENT

WATER･BUTYLENE GLYCOL･GLYCERIN･SILICA･GLYCERYL DIISOSTEARATE･ALCOHOL DENAT.･CAPRYLYL METHICONE･BEHENYL ALCOHOL･C30-45 ALKYL METHICONE･DIPROPYLENE GLYCOL･DIMETHICONE･AMMONIUM ACRYLOYLDIMETHYLTAURATE/BEHENETH-25 METHACRYLATE CROSSPOLYMER･XANTHAN GUM･TREHALOSE･TOCOPHERYL ACETATE･2-O-ETHYL ASCORBIC ACID･SCUTELLARIA BAICALENSIS ROOT EXTRACT･GLYCINE･PEG/PPG-14/7 DIMETHYL ETHER･THYMUS SERPYLLUM EXTRACT･GARCINIA MANGOSTANA BARK EXTRACT･PANAX GINSENG ROOT EXTRACT･FAGUS SYLVATICA BUD EXTRACT･AMINOETHANESULFINIC ACID･BUPLEURUM FALCATUM ROOT EXTRACT･ANGELICA ACUTILOBA ROOT EXTRACT･HYDROLYZED CONCHIOLIN PROTEIN･HYDROLYZED SILK･PERILLA OCYMOIDES LEAF EXTRACT･POLYQUATERNIUM-51･CRATAEGUS MONOGYNA FLOWER EXTRACT･SAXIFRAGA SARMENTOSA EXTRACT･GINKGO BILOBA LEAF EXTRACT･MENTHA PIPERITA (PEPPERMINT) LEAF EXTRACT･BEHENETH-20･C30-45 OLEFIN･STEARYL ALCOHOL･DISODIUM EDTA･CARBOMER･POTASSIUM HYDROXIDE･TOCOPHEROL･SODIUM METAPHOSPHATE･BHT･ALCOHOL･SODIUM METABISULFITE･THEANINE･SYZYGIUM JAMBOS LEAF EXTRACT･PHENOXYETHANOL･FRAGRANCE･IRON OXIDES･TITANIUM DIOXIDE･MICA･

Other information

- protect this product in this container from excessive heat and direct sunlight

Questions or Comments?

Call toll free 1-800-906-7503

PRINCIPAL DISPLAY PANEL - 50 mL Tube Carton

clé de peau

BEAUTÉ

UV PROTECTIVE CREAM n

50+

BROAD SPECTRYM

SPF 50+

SUNSCREEN

50mL NET WT. 1.8 OZ.